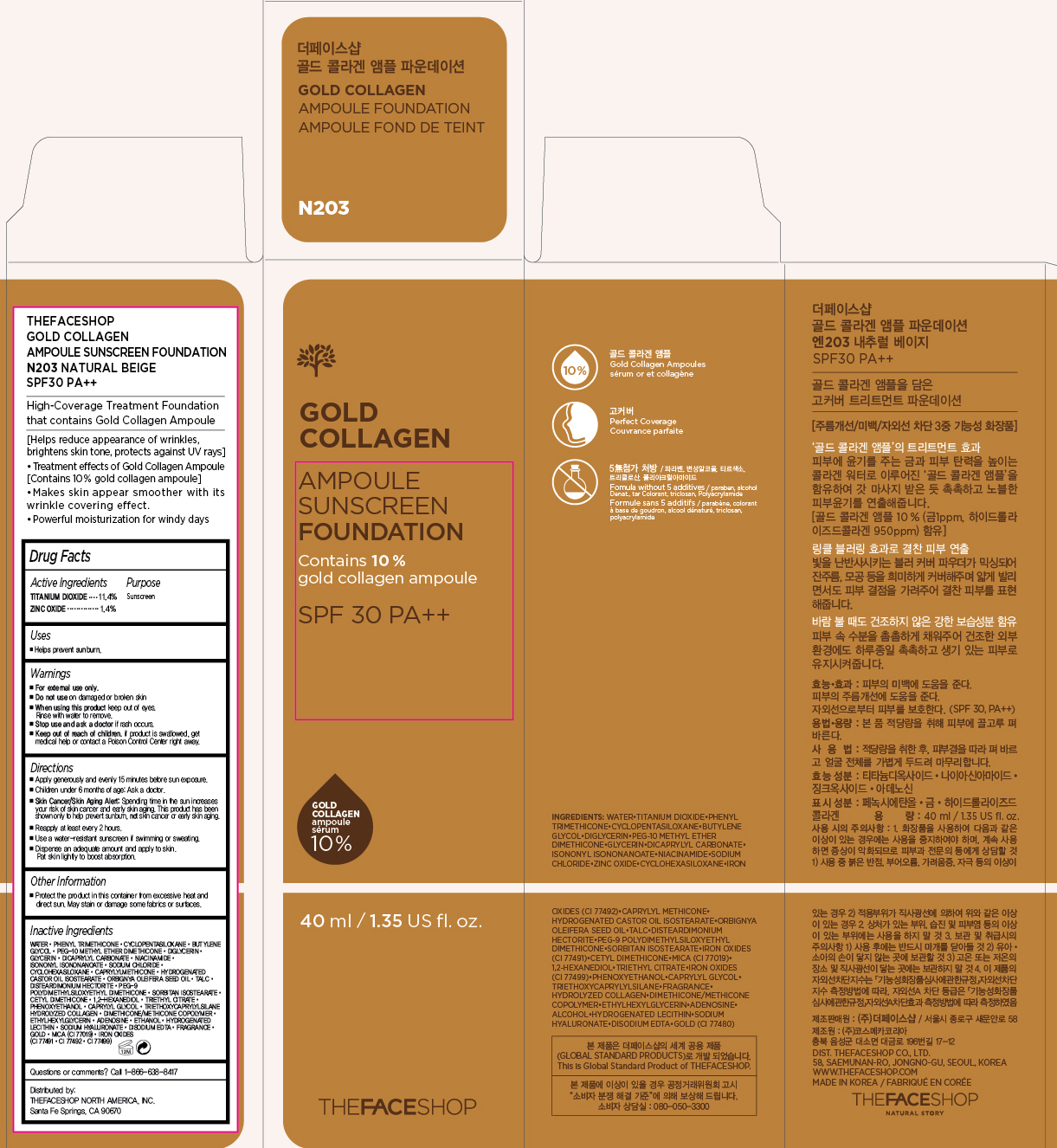 DRUG LABEL: GOLD COLLAGEN
NDC: 51523-258 | Form: POWDER
Manufacturer: THEFACESHOP CO., LTD.
Category: otc | Type: HUMAN OTC DRUG LABEL
Date: 20151231

ACTIVE INGREDIENTS: TITANIUM DIOXIDE 4.6 g/40 mL; ZINC OXIDE 0.6 g/40 mL
INACTIVE INGREDIENTS: WATER

TFS GOLD COLLAGEN AMPOULE FOUNDATION SPF30 PA++N203 34200258

Active Ingredients

Titanium Dioxide 11.4%

Zinc Oxide 1.4%

Uses

Helps prevent sunburn

Purpose

Sunscreen

Sunscreen

Warnings

For external use only.

Do not use on damaged or broken skin

When using this product keep out of eyes. Rinse with water to remove.

Stop use and ask a doctor if rash occurs.

Keep out of reach of children. If product is swallowed, get medical help or contact a Poison Control Center right away.

Directions

Apply generously and evenly 15 minutes before sun exposure.
Children under 6 months of age: Ask a doctor.
Skin Cancer/Skin Aging Alert: Spending time in the sun increases your risk of skin cancer and early skin aging. This product has been shown only to help prevent sunburn, not skin cancer or early skin aging.
Reapply at least every 2 hours.
Use a water-resistant sunscreen if swimming or sweating.

Dispense an adequate amount and apply to skin. Pat skin lightly to boost absorption.

Other Information

Protect the product in this container from excessive heat and direct sun.

May stain or damage some fabrics or surfaces.

Inactive Ingredients

Water, Phenyl Trimethicone, Cyclopentasiloxane, Butylene Glycol, PEG-10 Methyl Ether Dimethicone, Diglycerin, Glycerin, Dicaprylyl Carbonate, Niacinamide, Isononyl Isononanoate, Sodium Chloride, Cyclohexasiloxane, Caprylyl Methicone, Hydrogenated Castor Oil Isostearate, Orbignya Oleifera Seed Oil, Talc, Disteardimonium Hectorite, PEG-9 Polydimethylsiloxyethyl Dimethicone, Sorbitan Isostearate, Cetyl Dimethicone, 1,2-Hexanediol, Triethyl Citrate, Phenoxyethanol, Caprylyl Glycol, Triethoxycaprylylsilane Hydrolyzed Collagen, Dimethicone/Methicone Copolymer, Ethylhexylglycerin, Adenosine, Ethanol, Hydrogenated Lecithin, Sodium Hyaluronate, Disodium EDTA, Fragrance, Gold, Mica (CI 77019), Iron Oxides (CI 77491, CI 77492, CI 77499)

Questions

Questions or comments? Call 1-866-638-8417

Distributed by:

THEFACESHOP NORTH AMERICA, INC.

Santa Fe Springs, CA 90670

PACKAGE LABEL

THEFACESHOP GOLD COLLAGEN

AMPOULE SUNSCREEN FOUNDATION

N203 NATURAL BEIGE SPF30 PA+++

---------------------------------------------------

High-Coverage Treatment Foundation that contains Gold Collagen Ampoule

----------------------------------------------------

[Helps reduce appearance of wrinkles, brightens skin tone, protects against UV rays]

- Treatment effects of Gold Collangen Ampoule [Contains 10% gold collagen ampoule]
- Makes skin appear smoother with its wrinkle covering effect
- Powerful moisturization for windy days